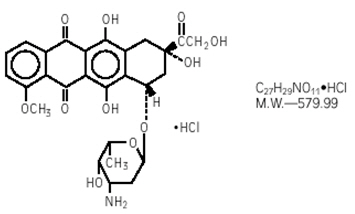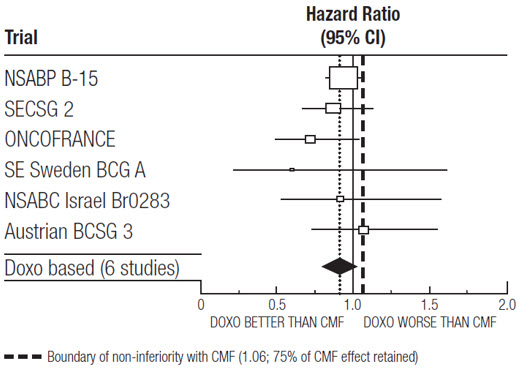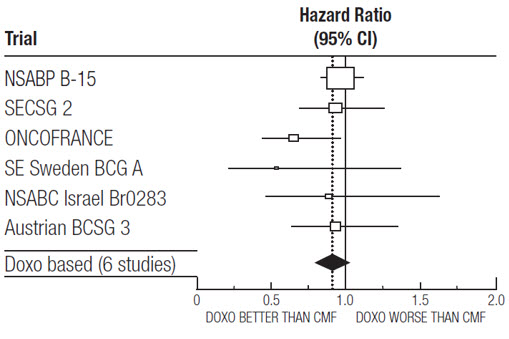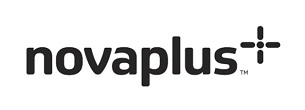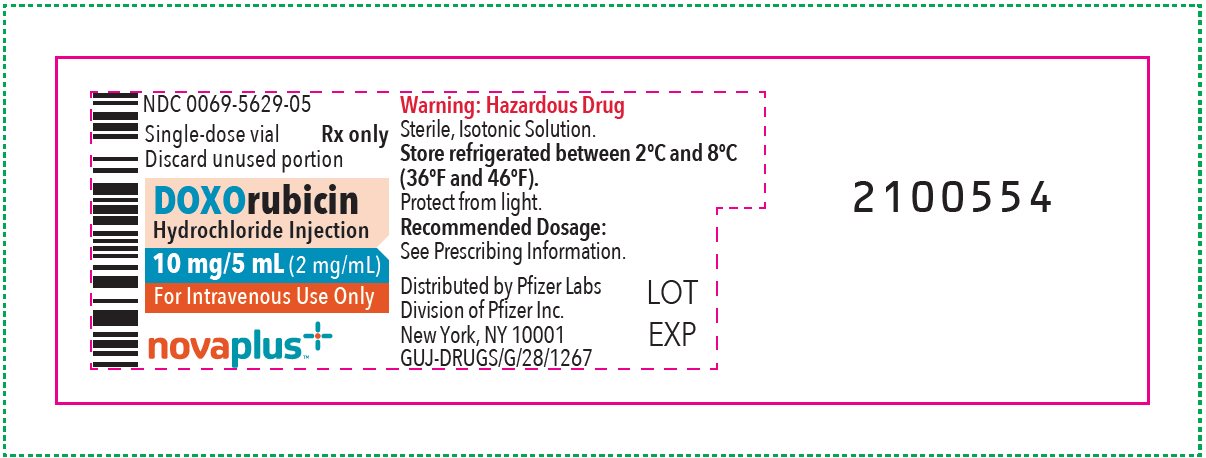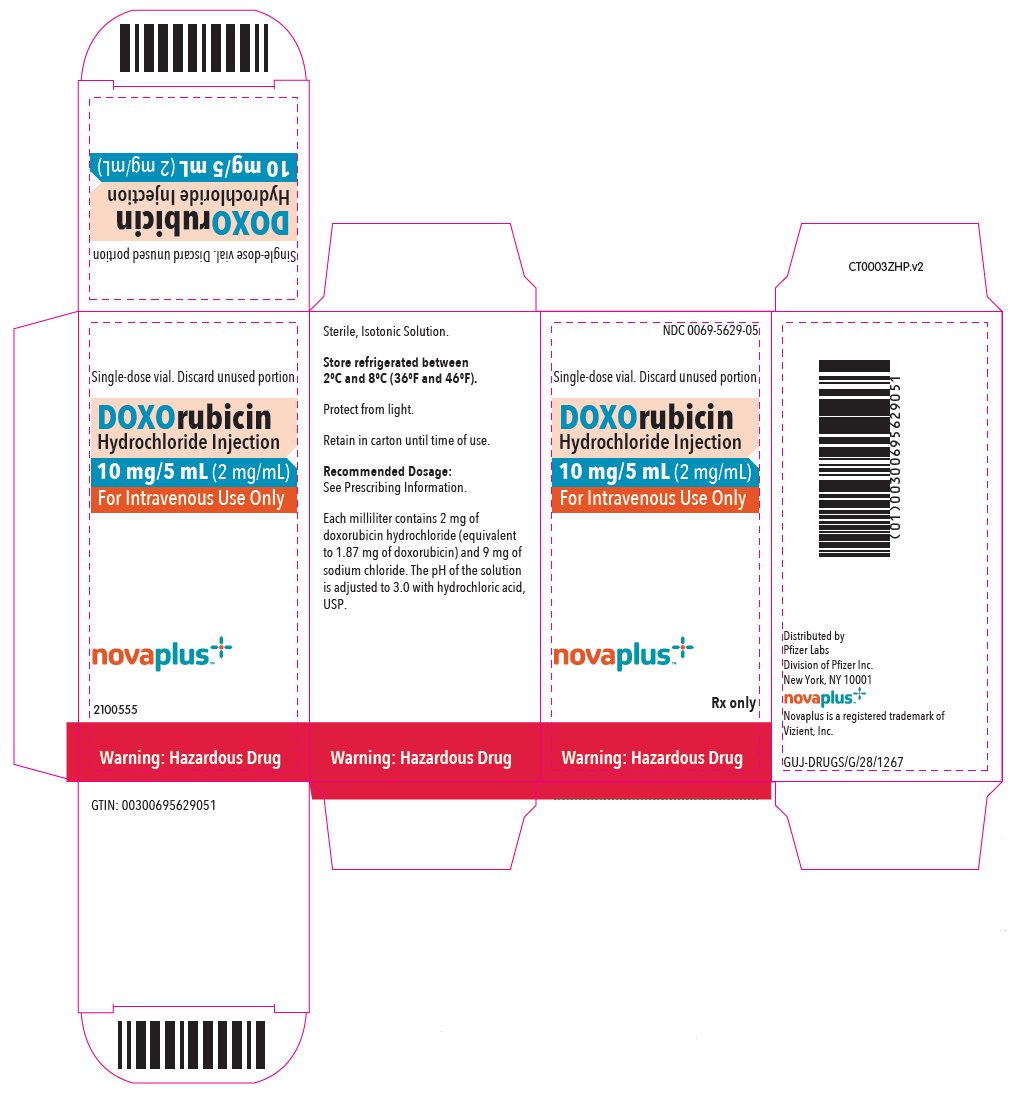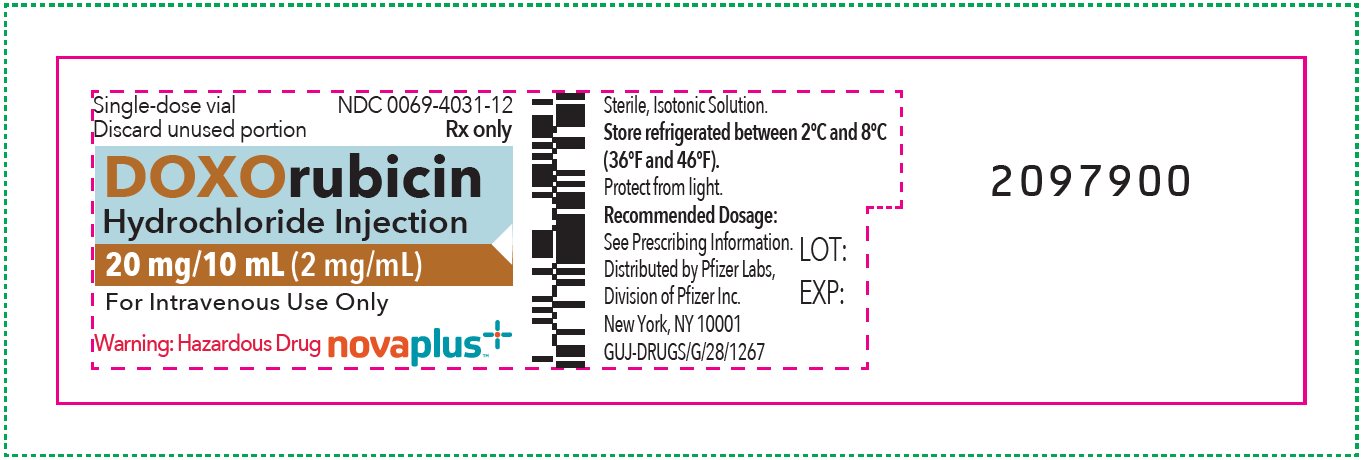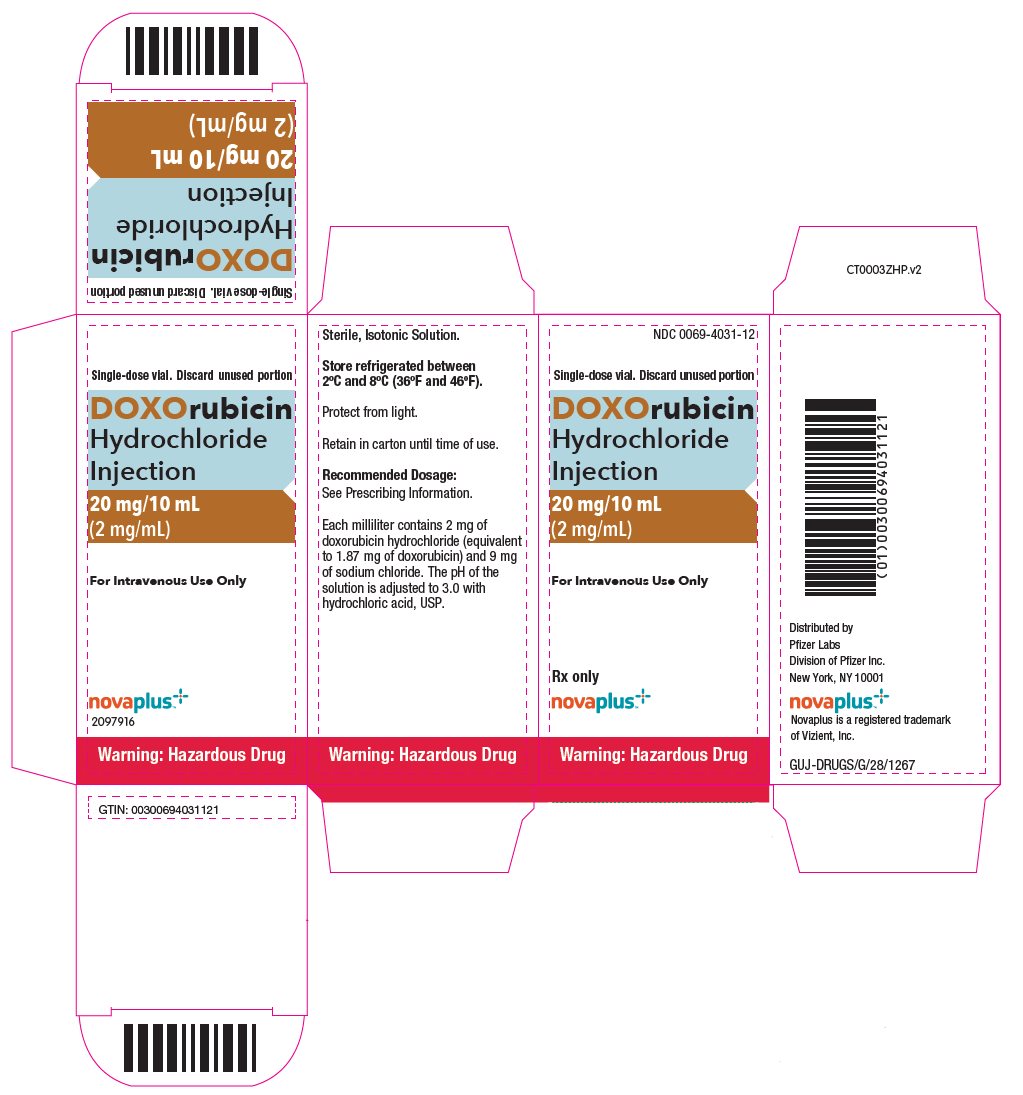 DRUG LABEL: Doxorubicin Hydrochloride
NDC: 0069-4031 | Form: INJECTION, SOLUTION
Manufacturer: Pfizer Laboratories Div Pfizer Inc
Category: prescription | Type: HUMAN PRESCRIPTION DRUG LABEL
Date: 20250331

ACTIVE INGREDIENTS: DOXORUBICIN HYDROCHLORIDE 2 mg/1 mL
INACTIVE INGREDIENTS: SODIUM CHLORIDE; HYDROCHLORIC ACID; WATER

HIGHLIGHTS OF PRESCRIBING INFORMATION

These highlights do not include all the information needed to use DOXORUBICIN HYDROCHLORIDE safely and effectively. See full prescribing information for DOXORUBICIN HYDROCHLORIDE.
DOXORUBICIN HYDROCHLORIDE injection, for intravenous use
Initial U.S. Approval: 1974

WARNING: CARDIOMYOPATHY, SECONDARY MALIGNANCIES, EXTRAVASATION AND TISSUE NECROSIS, and SEVERE MYELOSUPPRESSION

See full prescribing information for complete boxed warning.

- Cardiomyopathy: Myocardial damage can occur with doxorubicin hydrochloride with incidences from 1%–20% for cumulative doses from 300 mg/m^2 to 500 mg/m^2 when doxorubicin hydrochloride is administered every 3 weeks. The risk of cardiomyopathy is further increased with concomitant cardiotoxic therapy. Assess left ventricular ejection fraction (LVEF) before and regularly during and after treatment with doxorubicin hydrochloride. (5.1)
- Secondary Malignancies: Secondary acute myelogenous leukemia (AML) and myelodysplastic syndrome (MDS) occur at a higher incidence in patients treated with anthracyclines, including doxorubicin hydrochloride. (5.2)
- Extravasation and Tissue Necrosis: Extravasation of doxorubicin hydrochloride can result in severe local tissue injury and necrosis requiring wide excision and skin grafting. Immediately terminate the drug, and apply ice to the affected area. (5.3)
- Severe myelosuppression resulting in serious infection, septic shock, requirement for transfusions, hospitalization, and death may occur. (5.4)

1 INDICATIONS AND USAGE

Doxorubicin Hydrochloride Injection is an anthracycline topoisomerase inhibitor indicated:

- as a component of multi‑agent adjuvant chemotherapy for treatment of women with axillary lymph node involvement following resection of primary breast cancer (1.1)
- for the treatment of: acute lymphoblastic leukemia, acute myeloblastic leukemia, Hodgkin lymphoma, Non-Hodgkin lymphoma, metastatic breast cancer, metastatic Wilms' tumor, metastatic neuroblastoma, metastatic soft tissue sarcoma, metastatic bone sarcomas, metastatic ovarian carcinoma, metastatic transitional cell bladder carcinoma, metastatic thyroid carcinoma, metastatic gastric carcinoma, metastatic bronchogenic carcinoma (1.2)

2 DOSAGE AND ADMINISTRATION

- Single agent: 60 to 75 mg/m^2 given intravenously every 21 days (2.2)
- In combination: 40 to 75 mg/m^2 given intravenously every 21 to 28 days (2.2)
- Discontinue Doxorubicin Hydrochloride Injection in patients who develop signs or symptoms of cardiomyopathy (2.3)
- Reduce dose in patients with hepatic impairment (2.4)

3 DOSAGE FORMS AND STRENGTHS

Injection: 10 mg/5 mL, 20 mg/10 mL (3)

4 CONTRAINDICATIONS

- Severe myocardial insufficiency (4)
- Recent myocardial infarction (4)
- Severe persistent drug-induced myelosuppression (4)
- Severe hepatic impairment (4)
- Severe hypersensitivity to doxorubicin hydrochloride (4)

5 WARNINGS AND PRECAUTIONS

- Radiation-Induced Toxicity: Can be increased by the administration of Doxorubicin Hydrochloride Injection. Radiation recall can occur in patients who receive Doxorubicin Hydrochloride Injection after prior radiation therapy. (5.7)
- Embryo-Fetal Toxicity: Can cause fetal harm. Advise females of reproductive potential of the potential risk to a fetus and on the use of effective contraception. Advise males with female partners of reproductive potential to use effective contraception. Advise males with pregnant partners to use condoms. (5.8, 8.1, 8.3)

6 ADVERSE REACTIONS

The most common (>10%) adverse reactions are alopecia, nausea and vomiting. (6.1)

To report SUSPECTED ADVERSE REACTIONS, contact Pfizer, Inc. at 1-800-438-1985 or FDA at 1-800-FDA-1088 or www.fda.gov/medwatch.

7 DRUG INTERACTIONS

- Avoid concomitant use of doxorubicin hydrochloride with inhibitors and inducers of CYP3A4, CYP2D6, and/or P-gp (7.1)
- Do not administer doxorubicin hydrochloride in combination with trastuzumab due to increased risk of cardiac dysfunction (5.1, 7.2)

8 USE IN SPECIFIC POPULATIONS

- Lactation: Advise not to breastfeed (8.2)
- Females and Males of Reproductive Potential: May impair fertility (8.3)

FULL PRESCRIBING INFORMATION

WARNING: CARDIOMYOPATHY, SECONDARY MALIGNANCIES, EXTRAVASATION AND TISSUE NECROSIS, and SEVERE MYELOSUPPRESSION

- Cardiomyopathy: Myocardial damage, including acute left ventricular failure, can occur with doxorubicin hydrochloride. The risk of cardiomyopathy is proportional to the cumulative exposure with incidence rates from 1%–20% for cumulative doses ranging from 300 mg/m^2 to 500 mg/m^2 when doxorubicin hydrochloride is administered every 3 weeks. The risk of cardiomyopathy is further increased with concomitant cardiotoxic therapy. Assess left ventricular ejection fraction (LVEF) before and regularly during and after treatment with doxorubicin hydrochloride [see Warnings and Precautions (5.1)].
- Secondary Malignancies: Secondary acute myelogenous leukemia (AML) and myelodysplastic syndrome (MDS) occur at a higher incidence in patients treated with anthracyclines, including doxorubicin hydrochloride [see Warnings and Precautions (5.2)].
- Extravasation and Tissue Necrosis: Extravasation of doxorubicin hydrochloride can result in severe local tissue injury and necrosis requiring wide excision of the affected area and skin grafting. Immediately terminate the drug and apply ice to the affected area [see Warnings and Precautions (5.3)].
- Severe myelosuppression resulting in serious infection, septic shock, requirement for transfusions, hospitalization, and death may occur [see Warnings and Precautions (5.4)].

1 INDICATIONS AND USAGE

1.1 Adjuvant Breast Cancer

Doxorubicin Hydrochloride Injection is indicated as a component of multi-agent adjuvant chemotherapy for treatment of women with axillary lymph node involvement following resection of primary breast cancer.

1.2 Other Cancers

Doxorubicin Hydrochloride Injection is indicated for the treatment of

- acute lymphoblastic leukemia
- acute myeloblastic leukemia
- Hodgkin lymphoma
- non-Hodgkin lymphoma (NHL)
- metastatic breast cancer
- metastatic Wilms' tumor
- metastatic neuroblastoma
- metastatic soft tissue sarcoma
- metastatic bone sarcoma
- metastatic ovarian carcinoma
- metastatic transitional cell bladder carcinoma
- metastatic thyroid carcinoma
- metastatic gastric carcinoma
- metastatic bronchogenic carcinoma

2 DOSAGE AND ADMINISTRATION

2.1 Recommended Dosage for Adjuvant Breast Cancer

The recommended dosage of Doxorubicin Hydrochloride Injection is 60 mg/m^2 administered as an intravenous bolus on day 1 of each 21-day treatment cycle, in combination with cyclophosphamide, for a total of four cycles.

2.2 Recommended Dosage for Other Cancers

- The recommended dosage of Doxorubicin Hydrochloride Injection when used as a single agent is 60 mg/m^2 to 75 mg/m^2 intravenously every 21 days.
- The recommended dosage of Doxorubicin Hydrochloride Injection, when administered in combination with other chemotherapy drugs, is 40 mg/m^2 to 75 mg/m^2 intravenously every 21 to 28 days.
- Consider use of the lower Doxorubicin Hydrochloride Injection dose in the recommended dosage range or longer intervals between cycles for heavily pretreated patients, elderly patients, or obese patients.
- Cumulative doses above 550 mg/m^2 are associated with an increased risk of cardiomyopathy [see Warnings and Precautions (5.1)].

2.3 Dosage Modifications for Adverse Reactions

Cardiomyopathy

Discontinue Doxorubicin Hydrochloride Injection in patients who develop signs or symptoms of cardiomyopathy [see Warnings and Precautions (5.1)].

2.4 Dosage Modifications for Hepatic Impairment

Doxorubicin Hydrochloride Injection is contraindicated in patients with severe hepatic impairment (Child-Pugh Class C or serum bilirubin greater than 5 mg/dL) [see Contraindications (4)].

Dosage modifications for Doxorubicin Hydrochloride Injection in patients with elevated serum total bilirubin concentrations [see Warnings and Precautions (5.5), Use in Specific Populations (8.6)] are provided in Table 1.

Table 1. Recommended Dosage Modification for Elevated Serum Total Bilirubin
Serum Total Bilirubin Concentration | Dosage Modification
1.2–3 mg/dL | 50%
3.1–5 mg/dL | 75%
Greater than 5 mg/dL | Do not initiate Doxorubicin Hydrochloride Injection; discontinue Doxorubicin Hydrochloride Injection

2.5 Preparation and Administration

Doxorubicin Hydrochloride Injection is a hazardous drug. Follow applicable special handling and disposal procedures.^1

Preparation

Dilution of Doxorubicin Hydrochloride Injection

- Dilute Doxorubicin Hydrochloride Injection in 0.9% Sodium Chloride Injection, USP or 5% Dextrose Injection, USP.
- Protect from light following preparation until completion of infusion.
- Use within 1 hour. If not used within 1 hour, discard the diluted product.

Administration

- Visually inspect for particulate matter and discoloration prior to administration, whenever solution and container permit. Discard if the solution is discolored, cloudy, or contains particulate matter.

Administration by Intravenous Injection

- Administer diluted Doxorubicin Hydrochloride Injection as an intravenous injection through a central intravenous line or a secure and free-flowing peripheral venous line containing 0.9% Sodium Chloride Injection, USP, 0.45% Sodium Chloride Injection, USP, or 5% Dextrose Injection, USP.
- Administer intravenously over 3 to 10 minutes. Decrease the rate of infusion if erythematous streaking along the vein proximal to the site of infusion or facial flushing occur.

Administration by Continuous Intravenous Infusion

- Administer diluted Doxorubicin Hydrochloride Injection solution only through a central intravenous line. Decrease the rate of infusion if erythematous streaking along the vein proximal to the site of infusion or facial flushing occur.
- Protect from light from preparation for infusion until completion of infusion.

Management of Suspected Extravasation

Immediately discontinue Doxorubicin Hydrochloride Injection for burning or stinging sensation or other evidence indicating peri-venous infiltration or extravasation. Manage confirmed or suspected extravasation as follows:

- Do not remove the needle until attempts are made to aspirate extravasated fluid.
- Do not flush the line.
- Avoid applying pressure to the site.
- Apply ice to the site intermittently for 15 minutes, 4 times a day for 3 days.
- If the extravasation is in an extremity, elevate the extremity.
- In adults, consider administration of dexrazoxane [see Warnings and Precautions (5.3)].

Management of Contact with Skin or Eyes

Treat accidental contact with the skin or eyes immediately by copious lavage with water, or soap and water, or sodium bicarbonate solution. Do not abrade the skin by using a scrub brush. Seek medical attention.

Incompatibility with Other Drugs

Do not admix Doxorubicin Hydrochloride Injection with other drugs. If Doxorubicin Hydrochloride Injection is mixed with heparin or fluorouracil, a precipitate may form. Avoid contact with alkaline solutions which can lead to hydrolysis of doxorubicin hydrochloride.

3 DOSAGE FORMS AND STRENGTHS

Doxorubicin Hydrochloride Injection:

20 mg/10 mL clear red solution in a single‑dose vial

10 mg/5 mL clear red solution in a single‑dose vial

4 CONTRAINDICATIONS

Doxorubicin Hydrochloride Injection are contraindicated in patients with:

- Severe myocardial insufficiency [see Warnings and Precautions (5.1)]
- Recent (occurring within the past 4-6 weeks) myocardial infarction [see Warnings and Precautions (5.1)]
- Severe persistent drug-induced myelosuppression [see Warnings and Precautions (5.4)]
- Severe hepatic impairment (defined as Child Pugh Class C or serum bilirubin level greater than 5 mg/dL) [see Warnings and Precautions (5.5)]
- Severe hypersensitivity reaction to doxorubicin hydrochloride, including anaphylaxis [see Adverse Reactions (6.2)]

5 WARNINGS AND PRECAUTIONS

5.1 Cardiomyopathy and Arrhythmias

Cardiomyopathy

Doxorubicin hydrochloride can result in myocardial damage, including acute left ventricular failure. The risk of cardiomyopathy is generally proportional to the cumulative exposure. Include prior doses of other anthracyclines or anthracenediones in calculations of total cumulative dosage for doxorubicin hydrochloride. Cardiomyopathy may develop during treatment or up to several years after completion of treatment and can include decrease in LVEF and signs and symptoms of congestive heart failure (CHF). The probability of developing cardiomyopathy is estimated to be 1 to 2% at a total cumulative dose of 300 mg/m^2 of doxorubicin hydrochloride, 3 to 5% at a dose of 400 mg/m^2, 5 to 8% at a dose of 450 mg/m^2, and 6 to 20% at a dose of 500 mg/m^2, when doxorubicin hydrochloride is administered every 3 weeks. There is an additive or potentially synergistic increase in the risk of cardiomyopathy in patients who have received radiotherapy to the mediastinum or concomitant therapy with other known cardiotoxic agents, such as cyclophosphamide and trastuzumab.

Pericarditis and myocarditis have also been reported during or following doxorubicin hydrochloride treatment.

Assess left ventricular cardiac function (e.g., MUGA or echocardiogram) prior to initiation of Doxorubicin Hydrochloride Injection, during treatment to detect acute changes, and after treatment to detect delayed cardiotoxicity. Increase the frequency of assessments as the cumulative dose exceeds 300 mg/m^2. Use the same method of assessment of LVEF at all time points [see Use in Specific Populations (8.4)]. Discontinue Doxorubicin Hydrochloride Injection in patients who develop signs or symptoms of cardiomyopathy [see Dosage and Administration (2.3)].

Consider the use of dexrazoxane to reduce the incidence and severity of cardiomyopathy due to doxorubicin hydrochloride administration in patients who have received a cumulative doxorubicin hydrochloride dose of 300 mg/m^2 and who will continue to receive doxorubicin hydrochloride.

Arrhythmias

Doxorubicin hydrochloride can result in arrhythmias, including life-threatening arrhythmias, during or within a few hours after doxorubicin hydrochloride administration and at any time point during treatment. Tachyarrhythmias, including sinus tachycardia, premature ventricular contractions, and ventricular tachycardia, as well as bradycardia, can occur. Electrocardiographic changes, including non-specific ST-T wave changes, atrioventricular and bundle-branch block can also occur. These electrocardiographic changes may be transient and self-limited and may not require a dosage modification of doxorubicin hydrochloride.

5.2 Secondary Malignancies

The risk of developing secondary acute myelogenous leukemia (AML) and myelodysplastic syndrome (MDS) is increased following treatment with doxorubicin hydrochloride. Cumulative incidences ranged from 0.2% at five years to 1.5% at 10 years in two separate trials involving the adjuvant treatment of women with breast cancer. These leukemias generally occur within 1 to 3 years of treatment.

5.3 Extravasation and Tissue Necrosis

Extravasation of doxorubicin hydrochloride can cause severe local tissue injury manifesting as blistering, ulceration, and necrosis requiring wide excision of the affected area and skin grafting. Extravasation should be considered if a patient experiences a burning or stinging sensation or shows other evidence indicating peri-venous infiltration or extravasation; however, extravasation may be present in patients who do not experience a stinging or burning sensation or when blood return is present on aspiration of the infusion needle.

When given via a peripheral venous line, infuse Doxorubicin Hydrochloride Injection over 10 minutes or less to minimize the risk of thrombosis or perivenous extravasation.

If extravasation is suspected, immediately discontinue the intravenous injection or continuous intravenous infusion [see Dosage and Administration (2.5)]. Apply ice to the site intermittently for 15 minutes, 4 times a day for 3 days. In adults, if appropriate, administer dexrazoxane at the site of extravasation as soon as possible and within the first 6 hours after extravasation.

5.4 Severe Myelosuppression

Doxorubicin hydrochloride can cause myelosuppression. In Study 1, the incidence of severe myelosuppression was: grade 4 leukopenia (0.3%), grade 3 leukopenia (3%), and grade 4 thrombocytopenia (0.1%). A dose-dependent, reversible neutropenia is the predominant manifestation of myelosuppression from doxorubicin hydrochloride. When doxorubicin hydrochloride is administered every 21 days, the neutrophil count reaches its nadir 10 to 14 days after administration with recovery usually occurring by day 21.

Obtain complete blood counts prior to each treatment and carefully monitor patients during treatment for possible clinical complications due to myelosuppression. Delay next dose of Doxorubicin Hydrochloride Injection if severe myelosuppression has not improved. Consider dose reduction for patients with prolonged myelosuppression based on severity of reaction.

5.5 Use in Patients with Hepatic Impairment

The clearance of doxorubicin is decreased in patients with elevated serum bilirubin with an increased risk of toxicity [see Use in Specific Populations (8.6), Clinical Pharmacology (12.3)]. Doxorubicin Hydrochloride Injection is contraindicated in patients with severe hepatic impairment (defined as Child Pugh Class C or serum bilirubin level greater than 5 mg/dL) [see Contraindications (4)]. Reduce the dose of Doxorubicin Hydrochloride Injection in patients with serum bilirubin levels of 1.2 to 5 mg/dL [see Dosage and Administration (2.4)]. Obtain liver tests including ALT, AST, alkaline phosphatase, and bilirubin prior to and during therapy.

5.6 Tumor Lysis Syndrome

Doxorubicin hydrochloride can induce tumor lysis syndrome in patients with rapidly growing tumors. Evaluate blood uric acid levels, potassium, calcium, phosphate, and creatinine after initial treatment. Hydration, urine alkalinization, and prophylaxis with allopurinol to prevent hyperuricemia may minimize potential complications of tumor lysis syndrome.

5.7 Potentiation of Radiation Toxicity and Radiation Recall

Doxorubicin hydrochloride can increase radiation-induced toxicity to the myocardium, mucosa, skin, and liver. Radiation recall, including but not limited to cutaneous and pulmonary toxicity, can occur in patients who receive doxorubicin hydrochloride after prior radiation therapy.

5.8 Embryo-Fetal Toxicity

Based on findings in animals and its mechanism of action, Doxorubicin Hydrochloride Injection can cause fetal harm when administered to a pregnant woman; avoid the use of Doxorubicin Hydrochloride Injection during the 1st trimester. Available human data do not establish the presence or absence of major birth defects and miscarriage related to the use of doxorubicin hydrochloride during the 2nd and 3rd trimesters. Doxorubicin hydrochloride was teratogenic and embryotoxic in rats and rabbits at doses lower than the recommended human dose. Advise pregnant women of the potential risk to a fetus. Advise females of reproductive potential to use effective contraception during treatment with Doxorubicin Hydrochloride Injection and for 6 months after treatment. Advise males with female partners of reproductive potential to use effective contraception during treatment with Doxorubicin Hydrochloride Injection and for 3 months after treatment. Advise males with pregnant partners to use condoms during treatment with Doxorubicin Hydrochloride Injection and for at least 10 days after the final dose [see Use in Specific Populations (8.1, 8.3), Nonclinical Toxicology (13.1)].

6 ADVERSE REACTIONS

The following clinically significant adverse reactions are described elsewhere in the labeling.

- Cardiomyopathy and Arrhythmias [see Warnings and Precautions (5.1)]
- Secondary Malignancies [see Warnings and Precautions (5.2)]
- Extravasation and Tissue Necrosis [see Warnings and Precautions (5.3)]
- Severe Myelosuppression [see Warnings and Precautions (5.4)]
- Tumor Lysis Syndrome [see Warnings and Precautions (5.6)]
- Radiation Sensitization and Radiation Recall [see Warnings and Precautions (5.7)]

6.1 Clinical Trials Experience

Because clinical trials are conducted under widely varying conditions, adverse reaction rates observed in the clinical trials of a drug cannot be directly compared to rates in the clinical trials of another drug and may not reflect the rates observed in practice.

Breast Cancer

The safety data below were collected from 1492 women who received doxorubicin hydrochloride at a dose of 60 mg/m^2 and cyclophosphamide at a dose of 600 mg/m^2 (AC) every 3 weeks for 4 cycles for the adjuvant treatment of axillary lymph node positive breast cancer. The median number of cycles received was 4. Selected adverse reactions reported in this study are provided in Table 2. No treatment-related deaths were reported in patients on either arm of the study.

Table 2. Selected Adverse Reactions in Patients with Early Breast Cancer Involving Axillary Lymph Nodes
Adverse Reactions | AC [Includes pooled data from patients who received either AC for 4 cycles or AC for 4 cycles followed by CMF for 3 cycles] N = 1492 | Conventional CMF N = 739
Adverse Reactions | % | %
Alopecia | 92 | 71
Vomiting
Vomiting ≤12 hours | 34 | 25
Vomiting >12 hours | 37 | 12
Intractable | 5 | 2
Leukopenia
Grade 3 (1,000–1,999 /mm^3) | 3.4 | 9.4
Grade 4 (<1000 /mm^3) | 0.3 | 0.3
Shock, sepsis | 2 | 1
Systemic infection | 2 | 1
Cardiac dysfunction
Asymptomatic | 0.2 | 0.1
Transient | 0.1 | 0
Symptomatic | 0.1 | 0
Thrombocytopenia
Grade 3 (25,000–49,999 /mm^3) | 0 | 0.3
Grade 4 (<25,000 /mm^3) | 0.1 | 0
AC = doxorubicin hydrochloride, cyclophosphamide; CMF = cyclophosphamide, methotrexate, fluorouracil

6.2 Postmarketing Experience

The following adverse reactions have been identified during postapproval use of Doxorubicin Hydrochloride Injection. Because these reactions are reported voluntarily from a population of uncertain size, it is not always possible to reliably estimate their frequency or establish a causal relationship to drug exposure.

Cardiac – Cardiogenic shock

Cutaneous – Skin and nail hyperpigmentation, oncolysis, rash, itching, photosensitivity, urticaria, acral erythema, palmar plantar erythrodysesthesia

Gastrointestinal – Nausea, mucositis, stomatitis, necrotizing colitis, typhlitis, gastric erosions, gastrointestinal tract bleeding, hematochezia, esophagitis, anorexia, abdominal pain, dehydration, diarrhea, hyperpigmentation of the oral mucosa

Hypersensitivity – Anaphylaxis

Laboratory Abnormalities – Increased ALT, increased AST

Neurological – Peripheral sensory and motor neuropathy, seizures, coma

Ocular – Conjunctivitis, keratitis, lacrimation

Vascular – Phlebosclerosis, phlebitis/thrombophlebitis, hot flashes, thromboembolism

Other – Malaise/asthenia, fever, chills, weight gain

7 DRUG INTERACTIONS

7.1 Effect of Other Drugs on Doxorubicin Hydrochloride Injection

Inhibitors of CYP3A4, CYP2D6, and P-gp

Concomitant use of doxorubicin hydrochloride with inhibitors of CYP3A4, CYP2D6, or P-glycoprotein (P-gp), increased concentrations of doxorubicin, which may increase the incidence and severity of adverse reactions of doxorubicin hydrochloride. Avoid concomitant use of Doxorubicin Hydrochloride Injection with inhibitors of CYP3A4, CYP2D6, or P-gp.

Inducers of CYP3A4, CYP2D6, or P-gp

Concomitant use of doxorubicin hydrochloride with inducers of CYP3A4, CYP2D6, or P-gp may decrease the concentration of doxorubicin. Avoid concomitant use of Doxorubicin Hydrochloride Injection with inducers of CYP3A4, CYP2D6, or P-gp.

Paclitaxel

Paclitaxel, when given prior to doxorubicin hydrochloride, increases the plasma-concentrations of doxorubicin and its metabolites. Administer Doxorubicin Hydrochloride Injection prior to paclitaxel if used concomitantly.

7.2 Concomitant Use of Trastuzumab

Concomitant use of trastuzumab and doxorubicin hydrochloride results in an increased risk of cardiac dysfunction. Avoid concomitant administration of Doxorubicin Hydrochloride Injection and trastuzumab [see Warnings and Precautions (5.1)].

Patients receiving doxorubicin after stopping treatment with trastuzumab may also be at an increased risk of developing cardiotoxicity. Trastuzumab may persist in the circulation for up to 7 months. Therefore, avoid anthracycline-based therapy for up to 7 months after stopping trastuzumab when possible. If anthracyclines are used before this time, carefully monitor cardiac function.

7.3 Concomitant Use of Dexrazoxane

Do not administer dexrazoxane as a cardioprotectant at the initiation of doxorubicin hydrochloride-containing chemotherapy regimens. In a randomized trial in women with metastatic breast cancer, initiation of dexrazoxane with doxorubicin hydrochloride-based chemotherapy resulted in a significantly lower tumor response rate (48% vs. 63%; p = 0.007) and shorter time to progression compared to doxorubicin hydrochloride-based chemotherapy alone.

7.4 Concomitant Use of 6-Mercaptopurine

Doxorubicin hydrochloride may potentiate 6-mercaptopurine-induced hepatotoxicity. In 11 patients with refractory leukemia treated with 6-mercaptopurine (500 mg/m^2 intravenously daily for 5 days per cycle every 2–3 weeks) and doxorubicin hydrochloride (50 mg/m^2 intravenous once per cycle every 2–3 weeks) alone or with vincristine and prednisone, all developed hepatic dysfunction manifested by increased total serum bilirubin, alkaline phosphatase and aspartate aminotransferase.

8 USE IN SPECIFIC POPULATIONS

8.1 Pregnancy

Risk Summary

Based on findings in animals and its mechanism of action, Doxorubicin Hydrochloride Injection can cause fetal harm when administered to a pregnant woman; avoid the use of Doxorubicin Hydrochloride Injection during the 1st trimester. Available human data do not establish the presence or absence of major birth defects and miscarriage related to the use of doxorubicin hydrochloride during the 2nd and 3rd trimesters. Doxorubicin hydrochloride was teratogenic and embryotoxic in rats and embryotoxic in rabbits when administered during organogenesis at doses approximately 0.07 times (based on body surface area) the recommended human dose of 60 mg/m^2 (see Data). Advise pregnant women of the potential risk to a fetus.

In the U.S. general population, the estimated background risk of major birth defects and miscarriage in clinically recognized pregnancies is 2 to 4% and 15 to 20%, respectively.

Data

Animal Data

Doxorubicin hydrochloride was teratogenic and embryotoxic at doses of 0.8 mg/kg/day (about 0.07 times the recommended human dose based on body surface area) when administered during the period of organogenesis in rats. Teratogenicity and embryotoxicity were also seen using discrete periods of treatment. The most susceptible was the 6- to 9-day gestation period at doses of 1.25 mg/kg/day and greater. Characteristic malformations included esophageal and intestinal atresia, tracheo-esophageal fistula, hypoplasia of the urinary bladder, and cardiovascular anomalies. Doxorubicin hydrochloride was embryotoxic (increase in embryo‑fetal deaths) and abortifacient at 0.4 mg/kg/day (about 0.07 times the recommended human dose based on body surface area) in rabbits when administered during the period of organogenesis.

8.2 Lactation

Risk Summary

Doxorubicin was measured in the milk of one lactating patient after therapy with 70 mg/m^2 of doxorubicin hydrochloride given as a 15-minute intravenous infusion. The peak milk concentration at 24 hours after treatment was 4.4-fold greater than the corresponding plasma concentration. Doxorubicin was detectable in the milk up to 72 hours. There are no data on the effects of doxorubicin hydrochloride on the breastfed child or the effects on milk production. Because of the potential for serious adverse reactions in the breastfed child, advise women not to breastfeed during treatment with Doxorubicin Hydrochloride Injection and for 10 days after the final dose.

8.3 Females and Males of Reproductive Potential

Pregnancy Testing

Verify the pregnancy status of females of reproductive potential prior to initiating Doxorubicin Hydrochloride Injection.

Contraception

Females

Doxorubicin Hydrochloride Injection can cause fetal harm when administered to pregnant women [see Use in Specific Populations (8.1)]. Advise female patients of reproductive potential to use highly effective contraception during treatment with Doxorubicin Hydrochloride Injection and for 6 months after treatment. [see Use in Specific Populations (8.1)].

Males

Doxorubicin hydrochloride may damage spermatozoa and testicular tissue, resulting in possible genetic fetal abnormalities. Due to the potential for genotoxicity, advise males with female partners of reproductive potential to use effective contraception during treatment with Doxorubicin Hydrochloride Injection and for 3 months after treatment [see Nonclinical Toxicology (13.1)]. Males with pregnant partners should use condoms during treatment and for at least 10 days after the final dose [see Nonclinical Toxicology (13.1), Use in Specific Populations (8.1)].

Infertility

Females

In females of reproductive potential, Doxorubicin hydrochloride may cause infertility and result in amenorrhea. Premature menopause can occur. Recovery of menses and ovulation is related to age at treatment [see Nonclinical Toxicology (13.1)].

Males

Doxorubicin hydrochloride may result in oligospermia, azoospermia, and permanent loss of fertility. Sperm counts have been reported to return to normal levels in some men. This may occur several years after the end of therapy [see Nonclinical Toxicology (13.1)].

8.4 Pediatric Use

Based on postmarketing reports, pediatric patients treated with doxorubicin hydrochloride are at risk for developing late cardiovascular dysfunction. Risk factors include young age at treatment (especially < 5 years), high cumulative doses and receipt of combined modality therapy. Long-term periodic cardiovascular monitoring is recommended for all pediatric patients who have received doxorubicin hydrochloride. Doxorubicin hydrochloride, as a component of intensive chemotherapy regimens administered to pediatric patients, may contribute to prepubertal growth failure and may also contribute to gonadal impairment, which is usually temporary.

There are no recommended dose adjustments based on age. Doxorubicin clearance was increased in patients aged 2 years to 20 years as compared to adults, while doxorubicin clearance was similar in infants less than 2 years as compared to adults [see Clinical Pharmacology (12.3)].

8.5 Geriatric Use

Clinical experience in patients who were 65 years of age and older who received doxorubicin hydrochloride-based chemotherapy regimens for metastatic breast cancer showed no overall differences in safety and effectiveness compared with younger patients.

8.6 Hepatic Impairment

The clearance of doxorubicin was reduced in patients with elevated serum total bilirubin levels. Doxorubicin Hydrochloride Injection is contraindicated in patients with severe hepatic impairment (defined as Child Pugh Class C or serum bilirubin levels greater than 5 mg/dL) [see Contraindications (4)]. Reduce the dose of Doxorubicin Hydrochloride Injection in patients with serum total bilirubin levels greater than 1.2 mg/dL [See Dosage and Administration (2.4), Warnings and Precautions (5.5)].

10 OVERDOSAGE

Few cases of overdose have been described.

A 58-year-old man with acute lymphoblastic leukemia received 10-fold overdose of doxorubicin hydrochloride (300 mg/m^2) in one day. He was treated with charcoal filtration, hemopoietic growth factor (G-CSF), proton pump inhibitor and antimicrobial prophylaxis. The patient suffered sinus tachycardia, grade 4 neutropenia and thrombocytopenia for 11 days, severe mucositis and sepsis. The patient recovered completely 26 days after the overdose.

A 17-year-old girl with osteogenic sarcoma received 150 mg of doxorubicin hydrochloride daily for 2 days (intended dose was 50 mg per day for 3 days). The patient developed severe mucositis on days 4–7 after the overdose and chills and pyrexia on day 7. The patient was treated with antibiotics and platelets and recovered 18 days after overdose.

11 DESCRIPTION

Doxorubicin hydrochloride is an anthracycline topoisomerase inhibitor isolated from cultures of Streptomyces peucetius var. caesius. The chemical name of doxorubicin hydrochloride is 5,12-Naphthacenedione, 10-[(3-amino-2,3,6-trideoxy-α-L-lyxo-hexopyranosyl)oxy]-7,8,9,10-tetrahydro-6,8,11-trihydroxy-8-(hydroxylacetyl)-1-methoxy-, hydrochloride (8S-cis)-. The chemical structure of doxorubicin hydrochloride is:

Doxorubicin Hydrochloride Injection, for intravenous use is a clear red, sterile, isotonic aqueous solution provided in vials containing 10 mg/5 mL doxorubicin hydrochloride (equivalent to 9.37 mg of doxorubicin free base), 20 mg/10 mL doxorubicin hydrochloride (equivalent to 18.74 mg of doxorubicin free base). The drug product has demonstrated inherent antimicrobial activity suitable for a multiple dose presentation. Each milliliter of solution contains 2 mg of doxorubicin hydrochloride and 9 mg of sodium chloride. The pH of the solution is adjusted to 3.0 with hydrochloric acid, USP.

12 CLINICAL PHARMACOLOGY

12.1 Mechanism of Action

The cytotoxic effect of doxorubicin hydrochloride on malignant cells and its toxic effects on various organs are thought to be related to nucleotide base intercalation and cell membrane lipid binding activities of doxorubicin. Intercalation inhibits nucleotide replication and action of DNA and RNA polymerases. The interaction of doxorubicin with topoisomerase II to form DNA-cleavable complexes appears to be an important mechanism of doxorubicin hydrochloride cytocidal activity.

12.3 Pharmacokinetics

Pharmacokinetic studies conducted in patients with various types of tumors have shown that doxorubicin follows multiphasic disposition after intravenous injection. In four patients, doxorubicin demonstrated dose-independent pharmacokinetics across a dose range of 30 mg/m^2 to 70 mg/m^2.

Distribution

The distribution half-life is approximately 5 minutes. Steady-state distribution volume ranges from 809 L/m^2 to 1214 L/m^2. Binding of doxorubicin and its major metabolite, doxorubicinol, to plasma proteins is 75% and is independent of plasma concentration of doxorubicin up to 1.1 µg/mL.

Doxorubicin does not cross the blood brain barrier.

Elimination

Plasma clearance is ranges from 324 mL/min/m^2 to 809 mL/min/m^2. The terminal half-life is 20 hours to 48 hours.

Metabolism

Doxorubicin is a substrate of CYP3A4, CYP2D6, and P-gp.

Enzymatic reduction at the 7 position and cleavage of the daunosamine sugar yields aglycones which are accompanied by free radical formation, the local production of which may contribute to the cardiotoxic activity of doxorubicin hydrochloride.

Disposition of doxorubicinol in patients is formation rate limited, with the terminal half-life of doxorubicinol being similar to doxorubicin. The relative exposure of doxorubicinol, i.e., the ratio between the AUC of doxorubicinol and the AUC of doxorubicin is approximately 0.5.

Excretion

Plasma clearance is predominately by metabolism and biliary excretion. Approximately 40% of the dose appears in the bile in 5 days, while only 5% to 12% of the drug and its metabolites appear in the urine during the same time period. In urine, <3% of the dose was recovered as doxorubicinol over 7 days.

Specific Populations

Weight

Systemic clearance of doxorubicin is significantly reduced in obese women with ideal body weight greater than 130%. There was a significant reduction in clearance without any change in volume of distribution in obese patients when compared with normal patients with less than 115% ideal body weight.

Pediatric Patients

Following administration of doses ranging from 10 mg/m^2 to 75 mg/m^2 of doxorubicin hydrochloride to 60 patients ranging from 2 months to 20 years, doxorubicin clearance averaged 1443 ± 114 mL/min/m^2. Further analysis demonstrated that clearance in 52 patients ranging from 2 to 20 years (1540 mL/min/m^2) was increased compared with adults. However, clearance in infants younger than 2 years of age (813 mL/min/m^2) was decreased compared with older patients (ranging from 2 to 20 years) and approached the range of clearance values determined in adults [see Use in Specific Populations (8.4)].

Sex

A published clinical study involving 6 men and 21 women with no prior anthracycline therapy reported a significantly higher median doxorubicin clearance in men compared to women (1088 mL/min/m^2 versus 433 mL/min/m^2). However, the terminal half-life of doxorubicin was longer in men compared to women (54 versus 35 hours).

Patients with Hepatic Impairment

The clearance of doxorubicin and doxorubicinol was reduced in patients with elevated serum total bilirubin concentrations [see Dosage and Administration (2.4), Warnings and Precautions (5.5)].

13 NONCLINICAL TOXICOLOGY

13.1 Carcinogenesis, Mutagenesis, Impairment of Fertility

Doxorubicin hydrochloride treatment can increase the risk of secondary malignancies based on postmarketing reports [see Warnings and Precautions (5.2)]. Doxorubicin hydrochloride was mutagenic in the in vitro Ames assay, and clastogenic in multiple in vitro assays (CHO cell, V79 hamster cell, human lymphoblast, and SCE assays) and the in vivo mouse micronucleus assay.

Doxorubicin hydrochloride decreased fertility in female rats at the doses of 0.05 and 0.2 mg/kg/day (approximately 0.005 and 0.02 times the recommended human dose, based on body surface area).

A single intravenous dose of 0.1 mg/kg doxorubicin hydrochloride (approximately 0.01 times the recommended human dose based on body surface area) was toxic to male reproductive organs in animal studies, producing testicular atrophy, diffuse degeneration of the seminiferous tubules, and oligospermia/hypospermia in rats. Doxorubicin hydrochloride induces DNA damage in rabbit spermatozoa and dominant lethal mutations in mice.

14 CLINICAL STUDIES

14.1 Adjuvant Breast Cancer

The efficacy of doxorubicin hydrochloride-containing regimens for the post-operative, adjuvant treatment of surgically resected breast cancer was evaluated in a meta-analysis conducted by the Early Breast Cancer Trialists Collaborative Group (EBCTCG). The EBCTCG meta-analyses compared cyclophosphamide, methotrexate, and fluorouracil (CMF) to no chemotherapy (19 trials including 7523 patients) and doxorubicin hydrochloride-containing regimens with CMF as an active control (6 trials including 3510 patients). Data from the meta-analysis of trials comparing CMF to no therapy were used to establish the historical treatment effect size for CMF regimens. The major efficacy outcome measures were disease-free survival (DFS) and overall survival (OS).

Of the 3510 women (2157 received doxorubicin hydrochloride-containing regimens and 1353 received CMF treatment) with early breast cancer involving axillary lymph nodes included in the six trials from the meta-analyses, approximately 70% were premenopausal and 30% were postmenopausal.

At the time of the meta-analysis, 1745 first recurrences and 1348 deaths had occurred. The analyses demonstrated that doxorubicin hydrochloride-containing regimens retained at least 75% of the historical CMF adjuvant effect on DFS with a hazard ratio (HR) of 0.91 (95% CI: 0.82, 1.01) and on OS with a HR of 0.91 (95% CI: 0.81, 1.03). Efficacy results are provided in Table 3 and Figures 1 and 2.

Table 3. Summary of Randomized Trials Comparing Doxorubicin Hydrochloride-Containing Regimens Versus CMF in Meta-Analysis
Study (starting year) | Regimens | No. of Cycles | No. of Patients | Doxorubicin Hydrochloride-Containing Regimens vs. CMF HR [Hazard ratio of less than 1 indicates that the treatment with doxorubicin hydrochloride-containing regimens is associated with lower risk of disease recurrences or death compared to the treatment with CMF.] (95% CI)
Study (starting year) | Regimens | No. of Cycles | No. of Patients | DFS | OS
NSABP B-15 (1984) | AC | 4 | 1562 [Includes pooled data from patients who received either AC alone for 4 cycles, or who were treated with AC for 4 cycles followed by 3 cycles of CMF.] | 0.93 (0.82, 1.06) | 0.97 (0.83, 1.12)
NSABP B-15 (1984) | CMF | 6 | 776
SECSG 2 (1976) | FAC | 6 | 260 | 0.86 (0.66, 1.13) | 0.93 (0.69, 1.26)
SECSG 2 (1976) | CMF | 6 | 268
ONCOFRANCE (1978) | FACV | 12 | 138 | 0.71 (0.49, 1.03) | 0.65 (0.44, 0.96)
ONCOFRANCE (1978) | CMF | 12 | 113
SE Sweden BCG A (1980) | AC | 6 | 21 | 0.59 (0.22, 1.61) | 0.53 (0.21, 1.37)
SE Sweden BCG A (1980) | CMF | 6 | 22
NSABC Israel Br0283 (1983) | AVbCMF [Patients received alternating cycles of AVb and CMF.] | 4 6 | 55 | 0.91 (0.53, 1.57) | 0.88 (0.47, 1.63)
NSABC Israel Br0283 (1983) | CMF | 6 | 50
Austrian BCSG 3 (1984) | CMFVA | 6 | 121 | 1.07 (0.73, 1.55) | 0.93 (0.64, 1.35)
Austrian BCSG 3 (1984) | CMF | 8 | 124
Combined Studies | Doxorubicin Hydrochloride-Containing Regimen |  | 2157 | 0.91 (0.82, 1.01) | 0.91 (0.81, 1.03)
Combined Studies | CMF |  | 1353 | 0.91 (0.82, 1.01) | 0.91 (0.81, 1.03)
Abbreviations: DFS = disease free survival; OS = overall survival; AC = doxorubicin hydrochloride, cyclophosphamide; AVbCMF = doxorubicin hydrochloride, vinblastine, cyclophosphamide, methotrexate, fluorouracil; CMF = cyclophosphamide, methotrexate, fluorouracil; CMFVA = cyclophosphamide, methotrexate, fluorouracil, vincristine, doxorubicin hydrochloride; FAC = fluorouracil, doxorubicin hydrochloride, cyclophosphamide; FACV = fluorouracil, doxorubicin hydrochloride, cyclophosphamide, vincristine; HR = hazard ratio; CI = confidence interval

Figure 1. Meta-analysis of Disease-Free Survival

Figure 2. Meta-analysis of Overall Survival

15 REFERENCES

1. “Hazardous Drugs”. OSHA. http://www.osha.gov/SLTC/hazardousdrugs/index.html

16 HOW SUPPLIED/STORAGE AND HANDLING

Doxorubicin Hydrochloride Injection

Doxorubicin Hydrochloride Injection is a sterile, isotonic solution, available in single-dose ONCO-TAIN® glass vials:

Unit of Sale | Total Strength/Total Volume; (Concentration)
NDC 0069-4031-12; Carton of 1 Single-dose Vial | 20 mg/10 mL; (2 mg/mL)
NDC 0069-5629-05; Carton of 1 Single-dose Vial | 10 mg/5 mL; (2 mg/mL)

ONCO-TAIN® is the vial external protection system.

Retain in carton until contents are used. For single-dose ONCO-TAIN® glass vials, discard unused portion.

Storage

Store all vials at 2°C to 8°C (36°F to 46°F). Protect from light.

Storage of Doxorubicin Hydrochloride Injection under refrigerated conditions can result in the formation of a gelled product. Place gelled product at room temperature [15ºC to 30ºC (59ºF to 86ºF)] for 2 to 4 hours to return the product to a slightly viscous, mobile solution.

Handling and Disposal

Doxorubicin Hydrochloride Injection is a hazardous drug. Follow applicable special handling and disposal procedures.^1

17 PATIENT COUNSELING INFORMATION

Advise the patient to read the FDA-approved patient labeling (Patient Information).

Cardiomyopathy

Advise patients that Doxorubicin Hydrochloride Injection can cause irreversible myocardial damage and to contact a healthcare provider for symptoms of heart failure during or after treatment [see Warnings and Precautions (5.1)].

Secondary Malignancy

Advise patients of the increased risk of treatment-related leukemia [see Warnings and Precautions (5.2)].

Myelosuppression

Advise patients that Doxorubicin Hydrochloride Injection can reduce the absolute neutrophil count resulting in an increased risk of infection and to contact a healthcare provider for new onset fever or symptoms of infection [see Warnings and Precautions (5.4)].

Embryo-Fetal Toxicity

Advise pregnant women and females of reproductive potential of the potential risk to a fetus, and to inform their healthcare provider of a known or suspected pregnancy [see Warnings and Precautions (5.8), Use in Specific Populations (8.1)].

Advise females of reproductive potential to use effective contraception during treatment with Doxorubicin Hydrochloride Injection and for 6 months after treatment [see Warnings and Precautions (5.8), Use in Specific Populations (8.3)].

Advise patients that Doxorubicin Hydrochloride Injection may induce chromosomal damage in sperm, which may lead to loss of fertility and offspring with birth defects. Advise males with female partners of reproductive potential to use effective contraception during treatment with Doxorubicin Hydrochloride Injection and for 3 months after treatment [see Warnings and Precautions (5.8), Use in Specific Populations (8.3), Nonclinical Toxicology (13.1)].

Advise males with pregnant partners to use condoms during treatment with Doxorubicin Hydrochloride Injection and for at least 10 days after the final dose [see Use in Specific Populations (8.3)].

Lactation

Advise females not to breastfeed during treatment with Doxorubicin Hydrochloride Injection and for 10 days after the final dose [see Use in Specific Populations (8.2)].

Infertility

Advise females and males of the potential loss of fertility from Doxorubicin Hydrochloride Injection [see Use in Specific Populations (8.3)].

Gastrointestinal and Dermatologic Adverse Reactions

Advise patients that Doxorubicin Hydrochloride Injection can cause nausea, vomiting, diarrhea, mouth/oral pain and sores and to contact a healthcare provider should they develop any severe symptoms that prevent them from eating and drinking [see Adverse Reactions (6)]. Advise patients that Doxorubicin Hydrochloride Injection can cause alopecia [see Adverse Reactions (6.1)].

Administration

Advise patients that Doxorubicin Hydrochloride Injection can cause their urine to appear red for 1 to 2 days after administration.

This product’s labeling may have been updated. For the most current prescribing information, please visit www.pfizer.com.

Distributed by

Pfizer Labs

Division of Pfizer Inc.

New York, NY 10001

Novaplus is a registered trademark of Vizient, Inc.

LAB-1602-1.0

Patient Information

DOXORUBICIN (dok-suh-roo-buh-sin) HYDROCHLORIDE
injection, for intravenous use

What is the most important information I should know about Doxorubicin?

Doxorubicin may cause serious side effects including:

- Heart muscle problems. Doxorubicin can cause heart muscle damage that may lead to heart failure. Heart failure means your heart does not pump blood well. Heart failure is irreversible in some cases and can lead to death. Heart failure can happen during your treatment with Doxorubicin or months to years after stopping treatment. Your risk of heart muscle damage increases with higher total amounts of Doxorubicin that you receive in your lifetime. Your risk of heart failure is higher if you:
  - have other heart problems
  - have had or are currently receiving radiation therapy to your chest
  - have had treatment with certain other anti-cancer medicines
  - take other medicines that can have severe side effects on your heart
  Tell your healthcare provider if you get any of these symptoms of heart failure during or after treatment with Doxorubicin:

- extreme tiredness or weakness
- shortness of breath

- fast heartbeat
- swelling of your feet and ankles

Your healthcare provider will do tests to check the strength of your heart muscle before, during, and after your treatment with Doxorubicin.

- Heart rhythm problems. Doxorubicin can cause serious heart rhythm problems that may lead to death. This can happen during your infusion, within a few hours after your infusion or anytime during treatment with Doxorubicin. Tell your healthcare provider if you get any symptoms of heart rhythm problems, such as feeling as if your heart is beating fast, irregular or slow, or you feel lightheaded, dizzy, short of breath, chest discomfort or you faint.
- Risk of new cancers. You may have an increased risk of developing certain blood cancers called acute myelogenous leukemia (AML) or myelodysplastic syndrome (MDS) after treatment with Doxorubicin. Talk with your healthcare provider about your risk of developing new cancers if you receive Doxorubicin.
- Skin damage at or near the vein where Doxorubicin is given. Doxorubicin can damage the skin if it leaks out of the vein and might cause blisters, skin sores or severe tissue damage, which may require skin grafts. Tell your healthcare provider if you get burning or stinging during your infusion.
- Decreased blood cell counts. Doxorubicin can cause a decrease in neutrophils (a type of white blood cell important in fighting bacterial infections) and platelets (important for clotting and to control bleeding). This may lead to a serious infection, the need for blood transfusions, treatment in a hospital or death. Your healthcare provider will check your blood cell counts before each infusion and during treatment with Doxorubicin. Call your healthcare provider right away if you get a fever (temperature of 100.4°F or higher) or chills with shivering.

What is Doxorubicin?

Doxorubicin is a prescription medicine used to treat certain types of cancers. Doxorubicin may be used alone or along with other anti-cancer medicines.

Do not receive Doxorubicin if:

- you have had a recent heart attack (within the past 4 to 6 weeks) or have severe heart problems.
- your blood cell counts (platelets, red blood cells, and white blood cells) are very low because of prior chemotherapy.
- you have severe liver problems.
- you have had a severe allergic reaction to Doxorubicin.

Before you receive Doxorubicin, tell your healthcare provider about all of your medical conditions, including if you:

- have heart problems including heart failure.
- are currently receiving radiation therapy or plan to receive radiation to the chest.
- have liver problems.
- have had an allergic reaction to doxorubicin.
- are pregnant or plan to become pregnant. Doxorubicin can harm your unborn baby. You should not become pregnant during treatment with Doxorubicin. Tell your healthcare provider right away if you become pregnant or think you may be pregnant.
  Females who are able to become pregnant:
  - Your healthcare provider will check to see if you are pregnant before you start treatment with Doxorubicin.
  - You should use effective birth control (contraception) during treatment with Doxorubicin and for 6 months after treatment.
Males:
  1. Doxorubicin can affect your sperm and could cause birth defects.
  2. If you have a female partner who can become pregnant, you should use effective birth control during treatment with Doxorubicin and for 3 months after treatment.
  3. If you have a pregnant partner, you should use condoms during treatment with Doxorubicin and for at least 10 days after the final dose.
  4. Talk to your healthcare provider about birth control methods that may be right for you.
- are breastfeeding or plan to breastfeed. Doxorubicin can pass into your breast milk. Do not breastfeed during treatment with Doxorubicin and for 10 days after the final dose. Talk to your healthcare provider about the best way to feed your baby during this time.

Tell your healthcare provider about all the medicines you take, including prescription and over-the-counter medicines, vitamins, and herbal supplements.

How will I receive Doxorubicin?

- Doxorubicin will be given to you into your vein through an intravenous (IV) line.
- Your healthcare provider will do blood tests to check for side effects during treatment with Doxorubicin.
- Your healthcare provider may stop your treatment, change the timing of your treatment, or change the dose of your treatment if you have certain side effects while receiving Doxorubicin.

What are the possible side effects of Doxorubicin?

Doxorubicin may cause serious side effects, including:

- See “What is the most important information I should know about Doxorubicin?”

The most common side effects of Doxorubicin include:

- total hair loss (alopecia). Your hair may re-grow after your treatment.
- nausea
- vomiting

Other side effects:

- Red colored urine. You may have red colored urine for 1 to 2 days after your infusion of Doxorubicin. This is normal. Tell your healthcare provider if it does not stop in a few days, or if you see what looks like blood or blood clots in your urine.
- Call your healthcare provider if you have severe symptoms that prevent you from eating or drinking, such as:
  - nausea
  - vomiting
  - diarrhea
  - mouth pain or sores

Doxorubicin may cause fertility problems in males. This could affect your ability to father a child. Talk to your healthcare provider if this is a concern for you.

Doxorubicin may cause fertility problems in females. Your periods (menstrual cycle) may completely stop when you receive Doxorubicin. Your periods may or may not return following treatment. Early menopause has also happened. Talk to your healthcare provider if this is a concern for you.

These are not all of the possible side effects of Doxorubicin.

Call your doctor for medical advice about side effects. You may report side effects to FDA at 1-800-FDA-1088.

General information about the safe and effective use of Doxorubicin.

Medicines are sometimes prescribed for purposes other than those listed in a Patient Information leaflet.

You can ask your pharmacist or healthcare provider for information about Doxorubicin that is written for health professionals.

What are the ingredients in Doxorubicin?

Active ingredient: doxorubicin hydrochloride

Inactive ingredients for Doxorubicin Hydrochloride Injection: sodium chloride, and hydrochloric acid, USP.

Distributed by

Pfizer Labs

Division of Pfizer Inc.

New York, NY 10001

Novaplus is a registered trademark of Vizient, Inc.

LAB-1603-1.0

For more information, call 1-800-438-1985 or visit www.pfizer.com.

This Patient Information has been approved by the U.S. Food and Drug Administration.

Revised: 7/2024

PRINCIPAL DISPLAY PANEL - 10 mg/5 mL ONCO-TAIN® Label

NDC 0069-5629-05

Single-dose vial
Rx only

Discard unused portion

DOXOrubicin
Hydrochloride Injection

10 mg/5 mL (2 mg/mL)

For Intravenous Use Only

novaplusTM

PRINCIPAL DISPLAY PANEL - 10 mg/5 mL ONCO-TAIN® Carton

NDC 0069-5629-05

Single-dose vial. Discard unused portion

DOXOrubicin
Hydrochloride Injection

10 mg/5 mL (2 mg/mL)

For Intravenous Use Only

novaplusTM

Rx only

Warning: Hazardous Drug

PRINCIPAL DISPLAY PANEL - 20 mg/10 mL ONCO-TAIN® Label

Single-dose vial
NDC 0069-4031-12
Discard unused portion
Rx only

DOXOrubicin
Hydrochloride Injection

20 mg/10 mL (2 mg/mL)

For Intravenous Use Only

Warning: Hazardous Drug
novaplusTM

PRINCIPAL DISPLAY PANEL - 20 mg/10 mL ONCO-TAIN® Carton

NDC 0069-4031-12

Single-dose vial. Discard unused portion

DOXOrubicin
Hydrochloride
Injection

20 mg/10 mL
(2 mg/mL)

For Intravenous Use Only

Rx only

novaplusTM

Warning: Hazardous Drug